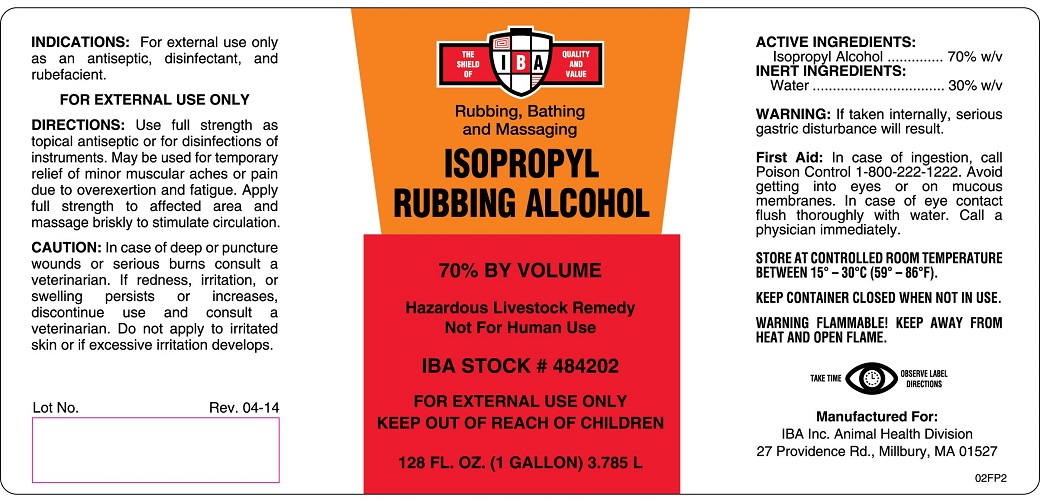 DRUG LABEL: ISOPROPYL RUBBING ALCOHOL
NDC: 29983-2651 | Form: LIQUID
Manufacturer: IBA, Inc.
Category: animal | Type: OTC ANIMAL DRUG LABEL
Date: 20141207

ACTIVE INGREDIENTS: ISOPROPYL ALCOHOL 70 L/100 L
INACTIVE INGREDIENTS: WATER 30 L/100 L

ISOPROPYL RUBBING ALCOHOL

INDICATIONS AND USAGE

Rubbing, Bathing and Massaging

70% BY VOLUME

Hazardous Livestock Remedy

Not For Human Use

FOR EXTERNAL USE ONLY

KEEP OUT OF REACH OF CHILDREN

INDICATIONS

For external use only as an antiseptic, disinfectant, and rubefacient

DIRECTIONS

Use full strength as topical antiseptic or for disinfections of instruments. May be used for temporary relief of minor muscular aches or pain due to overexertion and fatigue. Apply full strength to affected area, and massage briskly to stimulate circulation.

CAUTION

In case of deep or puncture wounds or serious burns consult a veterinarian. If redness, irritation, or swelling resists or increases, discontinue use and consult a veterinarian. Do not apply to irritated skin or if excessive irritation develops.

DOSAGE FORMS AND STRENGTHS

ACTIVE INGREDIENTS

Isopropyl Alcohol ................... 70% w/v

INERT INGREDIENTS

Water .................................. 30% w/v

WARNING

If taken internally, serious gastric disturbance will result.

First Aid

In case of ingestion, call Poison Control 1-800-222-1222. Avoid getting into eyes or on mucous membranes. In case of eye contact flush thoroughly with water. Call a physician immediately.

STORAGE AND HANDLING

STORE AT CONTROLLED ROOM TEMPERATURE BETWEEN 15o - 30oC (59o - 86oF).

KEEP CONTAINER CLOSED WHEN NOT IN USE.

WARNING FLAMMABLE: KEEP AWAY FROM HEAT AND OPEN FLAME.

TAKE TIME OBSERVE LABEL DIRECTIONS.